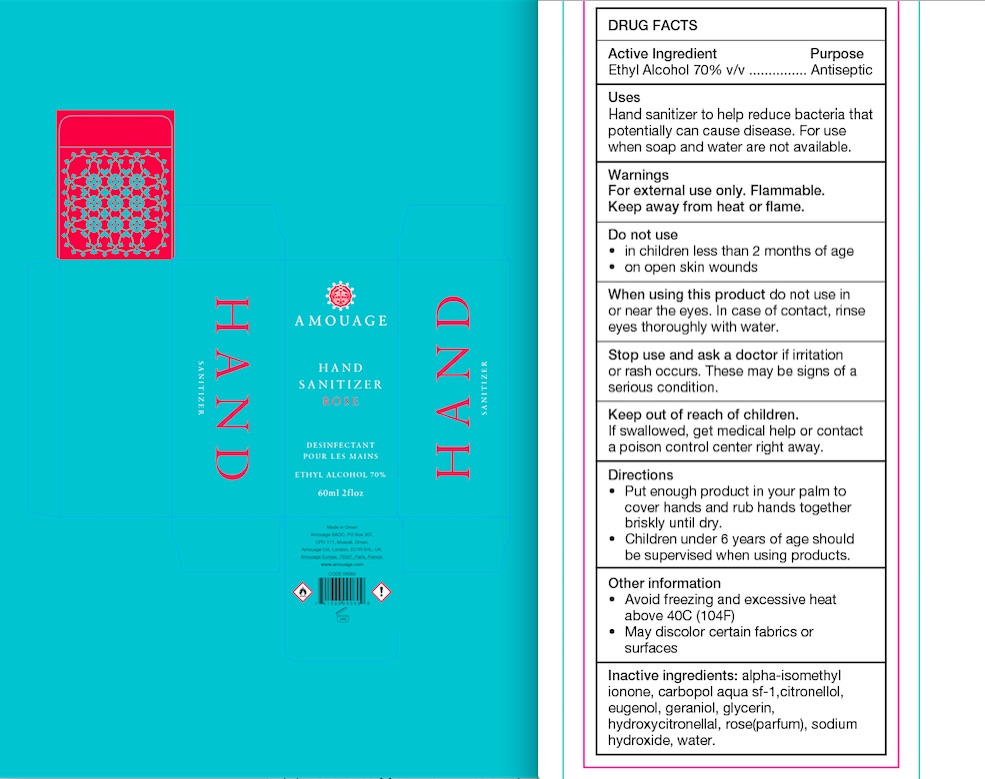 DRUG LABEL: AMOUAGE
NDC: 79809-111 | Form: GEL
Manufacturer: AMOUAGE SAOC
Category: otc | Type: HUMAN OTC DRUG LABEL
Date: 20211110

ACTIVE INGREDIENTS: ALCOHOL 70 mL/100 mL
INACTIVE INGREDIENTS: .BETA.-CITRONELLOL, (R)-; ROSE OIL; HYDROXYCITRONELLAL; GERANIOL; EUGENOL; METHACRYLIC ACID - ETHYL ACRYLATE COPOLYMER (4500 MPA.S); GLYCERIN; SODIUM HYDROXIDE; WATER; ISOMETHYL-.ALPHA.-IONONE

AMOUAGE Sanitizer Gel

Active Ingredient(s)

Alcohol 70% v/v. Purpose: Antiseptic

Purpose

Antiseptic, Hand Sanitizer

Use

Hand Sanitizer to help reduce bacteria that potentially can cause disease. For use when soap and water are not available.

Warnings

For external use only. Flammable. Keep away from heat or flame

Do not use

- in children less than 2 months of age
- on open skin wounds

When using this product keep out of eyes, ears, and mouth. In case of contact with eyes, rinse eyes thoroughly with water.
Stop use and ask a doctor if irritation or rash occurs. These may be signs of a serious condition.
Keep out of reach of children. If swallowed, get medical help or contact a Poison Control Center right away.

Stop use and ask a doctor if irritation or rash occurs. These may be signs of a serious condition.

Keep out of reach of children. If swallowed, get medical help or contact a Poison Control Center right away.

Directions

- Put enough product in your palm to cover hands and rub hands together briskly until dry
- Supervise children under 6 years of age when using this product to avoid swallowing.

Other information

Avoid freezing and excessive heat above 40C (104F)

May discolor certain fabrics or surfaces

Inactive ingredients

alpha-isomethyl ionone, carbopol aqua sf-1, citronellol, eugenol, geraniol, glycerin, hydroxycitronellal, rose (as parfum), sodium hydroxide, purified water

Package Label - Principal Display Panel

60 mL NDC:79809-111-11